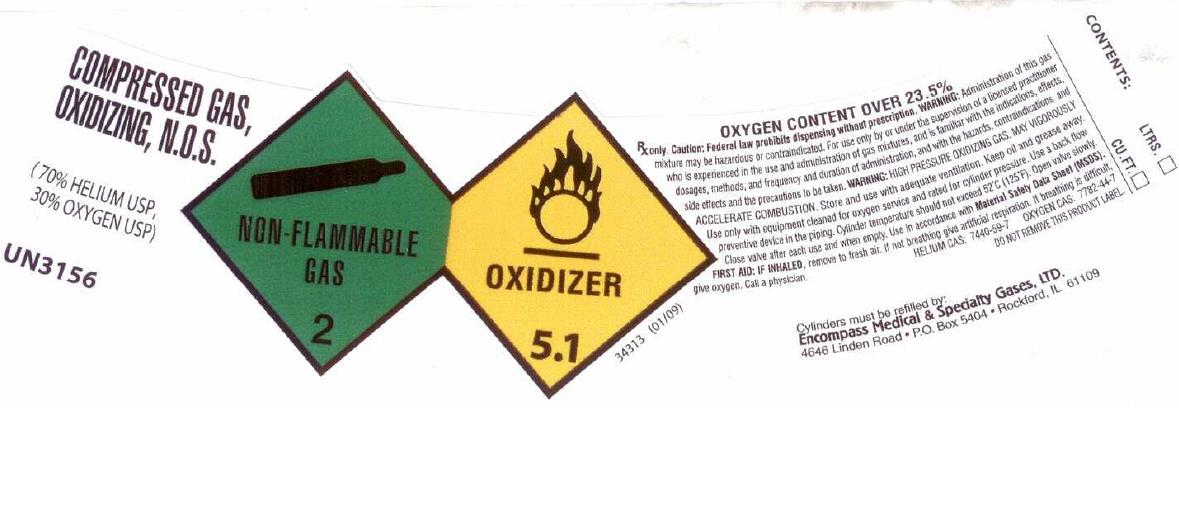 DRUG LABEL: Helium Oxygen Mix
NDC: 48883-007 | Form: GAS
Manufacturer: Encompass Medical & Specialty Gases Ltd
Category: prescription | Type: HUMAN PRESCRIPTION DRUG LABEL
Date: 20111229

ACTIVE INGREDIENTS: Helium 500 mL/1 L; Oxygen 500 mL/1 L

Helium Oxygen Mix Label

PACKAGE LABEL

COMPRESSED GAS , OXIDIZING, N.O.S. (70% HELIUM USP, 30% OXYGEN USP) UN 3156
NON-FLAMMABLE GAS 2 OXIDIZER 5.1
34313 (01/09) OXYGEN CONTENT OVER 23.5%
Rx only. CAUTION: Federal law prohibits dispensing without prescription. WARNING: Administration of this gas may be hazardous or contraindicated. For use only by or under supervision of a licensed practitioner who is experienced in the use and administration of gas mixtures, and is familiar with the indications, effects, dosages, methods, and frequency and duration of administration, and with the hazards, contraindications, and side effects and the precautions to be taken. WARNING: HIGH PRESSURE OXIDIZING GAS. MAY VIGOROUSLY ACCELERATE COMBUSTION. Store and use with adequate ventilation. Keep oil and grease away. Use only with equipment cleaned for oxygen service and rated for cylinder pressure. Use a back flow preventive device in the piping. Cylinder temperatures should not exceed 52C (125F). Open valve slowly. Close valve after each use and when empty. Use in accordance with the Material Safety Data Sheet (MSDS). FIRST AID: IF INHALED, remove to fresh air. If not breathing, give artificial respiration. If breathing is difficult, give oxygen. Call a physician. HELIUM CAS: 7440-59-7 OXYGEN CAS: 7782-44-7
DO NOT REMOVE THIS PRODUCT LABEL.
Cylinders must be refilled by:
Encompass Medical and Specialty Gases, LTD. 4646 Linden Road P.O. Box 5404 Rockford, IL 61109
CONTENTS: LTRS CU. FT.